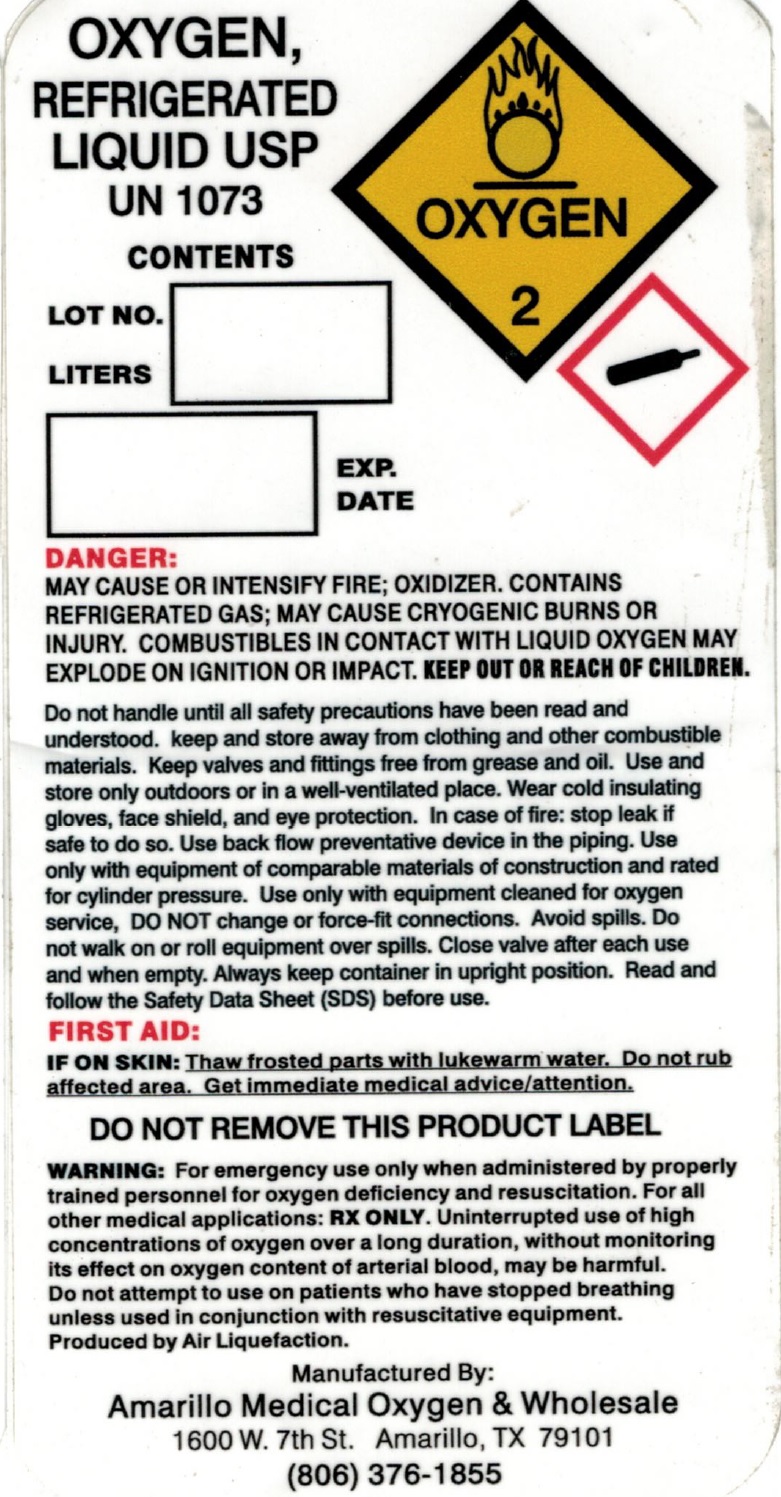 DRUG LABEL: Oxygen
NDC: 62137-001 | Form: LIQUID
Manufacturer: AMO Medical Oxygen, Inc.
Category: prescription | Type: HUMAN PRESCRIPTION DRUG LABEL
Date: 20201019

ACTIVE INGREDIENTS: OXYGEN 1000 g/1 L

Oxygen-Liquid